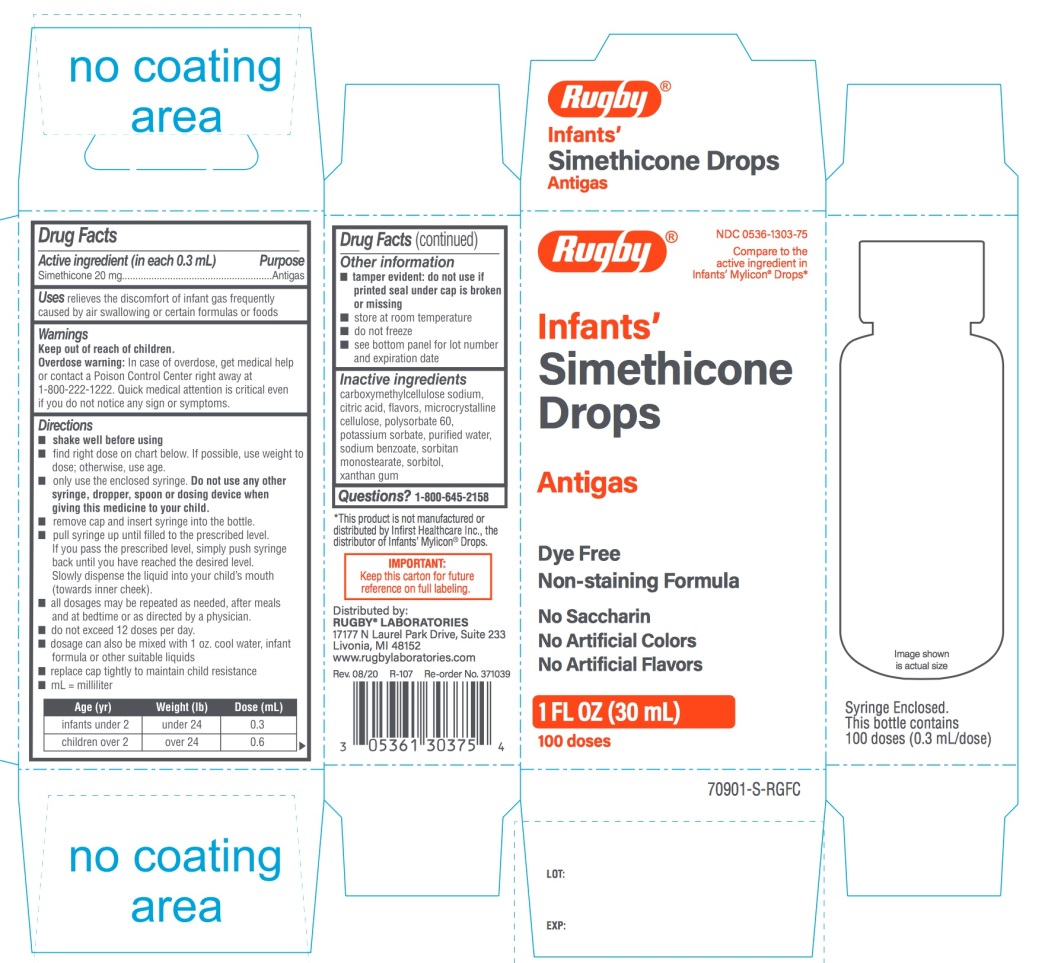 DRUG LABEL: Infants
NDC: 0536-1303 | Form: SUSPENSION/ DROPS
Manufacturer: RUGBY LABORATORIES
Category: otc | Type: HUMAN OTC DRUG LABEL
Date: 20251025

ACTIVE INGREDIENTS: DIMETHICONE, UNSPECIFIED 20 mg/0.3 mL
INACTIVE INGREDIENTS: CARBOXYMETHYLCELLULOSE SODIUM, UNSPECIFIED; ANHYDROUS CITRIC ACID; MICROCRYSTALLINE CELLULOSE; POLYSORBATE 60; POTASSIUM SORBATE; WATER; SODIUM BENZOATE; SORBITAN MONOSTEARATE; SORBITOL; XANTHAN GUM

Rugby®Infants’ Gas Relief Simethicone Drops

Active ingredient (in each 0.3 mL)

Simethicone 20 mg

Purpose

Antigas

Uses

relieves the discomfort of infant gas frequently caused by air swallowing or certain formulas or foods

Directions

- shake well before using
- find right dose on chart below. If possible, use weight to dose; otherwise, use age.
- only use the enclosed syringe. Do not use other syringe, dropper, spoon or dosing device when giving this medicine to your child.
- remove cap and insert syringe into the bottle.
- pull syringe up until filled to the prescribed level, simply push syringe back until you have reached the described level. Slowly dispense the liquid into your child’s mouth (towards inner cheek).
- all dosages may be repeated as needed, after meals and at bedtime or as directed by a physician.
- do not exceed 12 doses per day.
- dosage can also be mixed with 1 oz. cool water, infant formula or other suitable liquids.
- Replace cap tightly to maintain child resistance
- mL = milliliter

Age (yr) | Weight (lb) | Dose (mL)
infants under 2 | under 24 | 0.3
children over 2 | over 24 | 0.6

Other information

- tamper evident: do not use if printed seal under cap is broken or missing
- Store at room temperature
- do not freeze
- see bottom panel for lot number and expiration date

Inactive ingredients

carboxymethylcellulose sodium, citric acid, flavors, microcrystalline cellulose, polysorbate 60, potassium sorbate, purified water, sodium benzoate, sorbitan monostearate, sorbitol, xanthan gum

Questions or comments?

1-800-645-2158

Principal Display Panel

Rugby®

Compare to the active ingredient in Infants’ Mylicon®Drops*

NDC 0536-1303-75

Infants’

Simethicone Drops

Antigas

- Dye-free
- Non-staining formula
- No Saccharin
- No Artificial Color
- No Artificial Flavor

1 FL OZ (30 mL) 100 DOSES

Distributed by:

RUGBY LABORATORIES

17177 N Laurel Park Drive, Suite 233

Livonia, MI 48152

www.rugbylaboratories.com

Syringe Enclosed. This bottle contains 100 doses (0.3 mL/dose)

*This product is not manufactured or distributed by Infirst Healthcare Inc., the distributor of Infants’ MYLICON®Drops.